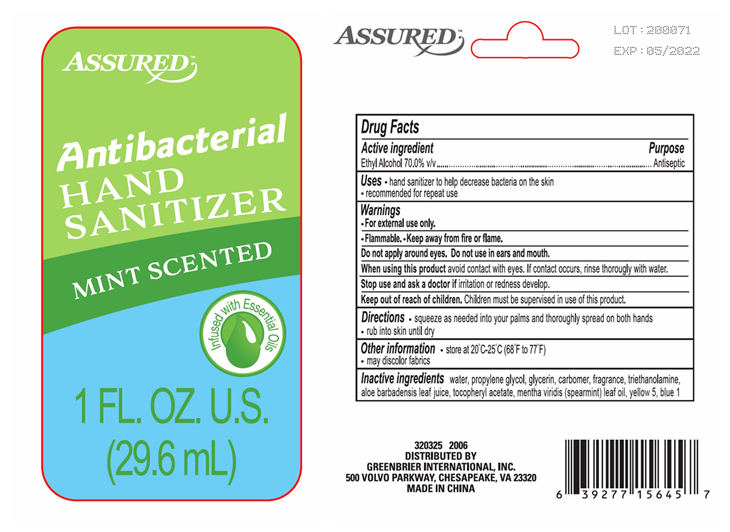 DRUG LABEL: MINT SCENTED 1OZ HAND SANITIZER
NDC: 33992-8954 | Form: GEL
Manufacturer: Greenbrier International, Inc.
Category: otc | Type: HUMAN OTC DRUG LABEL
Date: 20200510

ACTIVE INGREDIENTS: ALCOHOL 70 mL/100 mL
INACTIVE INGREDIENTS: SPEARMINT OIL; WATER; GLYCERIN; PROPYLENE GLYCOL; CARBOMER 940; ALPHA-TOCOPHEROL ACETATE; TROLAMINE; FD&C YELLOW NO. 5; ALOE VERA LEAF; FD&C BLUE NO. 1

MINT SCENTED 1OZ HAND SANITIZER

Drug Facts

Active Ingredient

Ethyl Alcohol 70.0% v/v

Purpose
Antiseptic

Uses

- hand sanitizer to help decrease bacteria on the skin
- recommended for repeat use

Warnings

For external use only.

Flammable.

Keep away from fire or flame.

Do not apply around eyes.

Do not use in ears and mouth

When using this product avoid contact with eyes. If contact occurs, rinse thorougly with water.

Stop use and ask a doctor if irritation or redness develop.

Keep out of reach of children. Children must be supervised in use of this product.

Directions

- pump as needed in your palms and thoroughly spread on both hands.
- rub into skin until dry.

Other Information

- Store at 20 degrees - 25 degrees C (68 degrees to 77 degrees)
- may discolor fabrics.

Inactive Ingredients
water, propylene glycol, glycerin, carbomer, fragrance, triethanolamine, aloe barbadensis leaf juice, tocopheryl acetate, mentha viridis (spearmint) leaf oil, yellow 5, blue 1

INDICATIONS AND USAGE

DISTRIBUTED BY:

GREENBRIER INTERNATIONAL, INC.
500 VOLVO PARKWAY, CHESAPEAKE, VA 23320
MADE IN CHINA